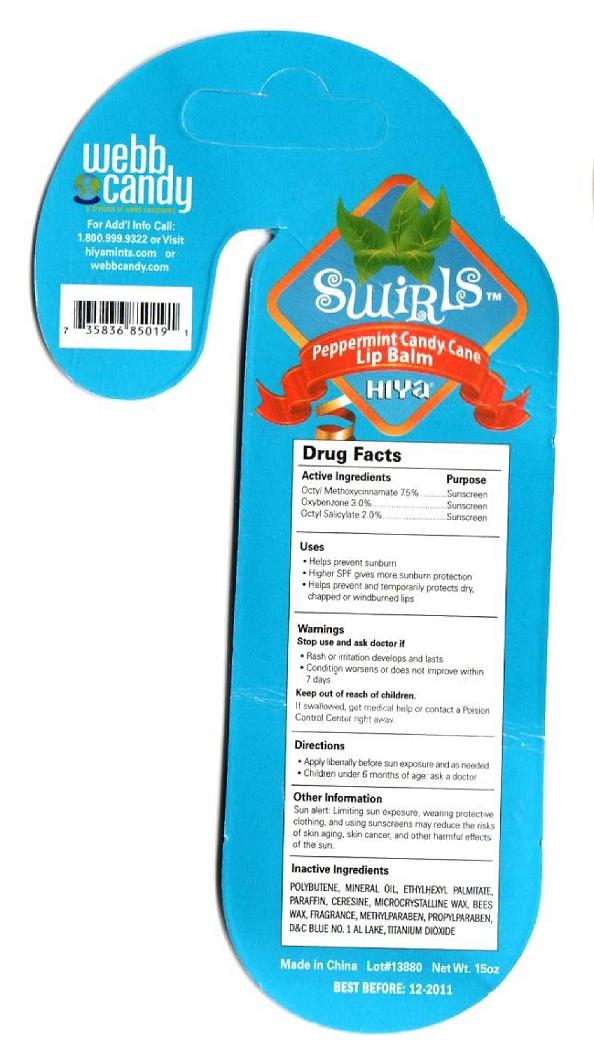 DRUG LABEL: Webb Candy
NDC: 49701-9000 | Form: LIPSTICK
Manufacturer: Webb Candy
Category: otc | Type: HUMAN OTC DRUG LABEL
Date: 20090916

ACTIVE INGREDIENTS: OCTINOXATE 7.5 g/100 g; OXYBENZONE 3 g/100 g; OCTISALATE 2 g/100 g
INACTIVE INGREDIENTS: MINERAL OIL; ETHYLHEXYL PALMITATE; PARAFFIN; WAX, YELLOW; METHYLPARABEN; PROPYLPARABEN; FD&C BLUE NO. 1; TITANIUM DIOXIDE

Webb Candy Peppermint Candy Cane Lip Balm

Active ingredients Purpose
Octyl Methoxycinnamate 7.5 percent Sunscreen
Oxybenzone 3.0 percent Sunscreen
Octyl Salicylate 2.0 percent Sunscreen

Uses
- Helps prevent sunburn
- Higher SPF gives more sunburn protection
- Helps prevent and temporarily protects dry, chapped or windburned lips

Stop use and ask a doctor if
- rash or irritation develops and lasts
- condition worsens or does not improve within 7 days

KEEP OUT OF REACH OF CHILDREN

If swallowed, get medical help or contact a Poison Control Center right away.

Directions
- Apply liberally before sun exposure and as needed
- Children under 6 months of age, ask a doctor

Other Information
Sun alert. Limiting sun exposure, wearing protective
clothing, and using sunscreens may reduce the risks
of skin aging, skin cancer, and other harmful effects
of the sun.

Inactive Ingredients
POLYBUTENE, MINERAL OIL, ETHYLHEXYL PALMITATE,
PARAFFIN, CERESINE, MICROCRYSTALLINE WAX, BEES
WAX, FRAGRANCE, METHYLPARABEN, PROPYLPARABEN,
D AND C BLUE NO. 1 AL LAKE, TITANIUM DIOXIDE

QUESTIONS

For Add'l Info Call:
1.800.999.9322 or Visit
hiyamints.com or
webbcandy.com